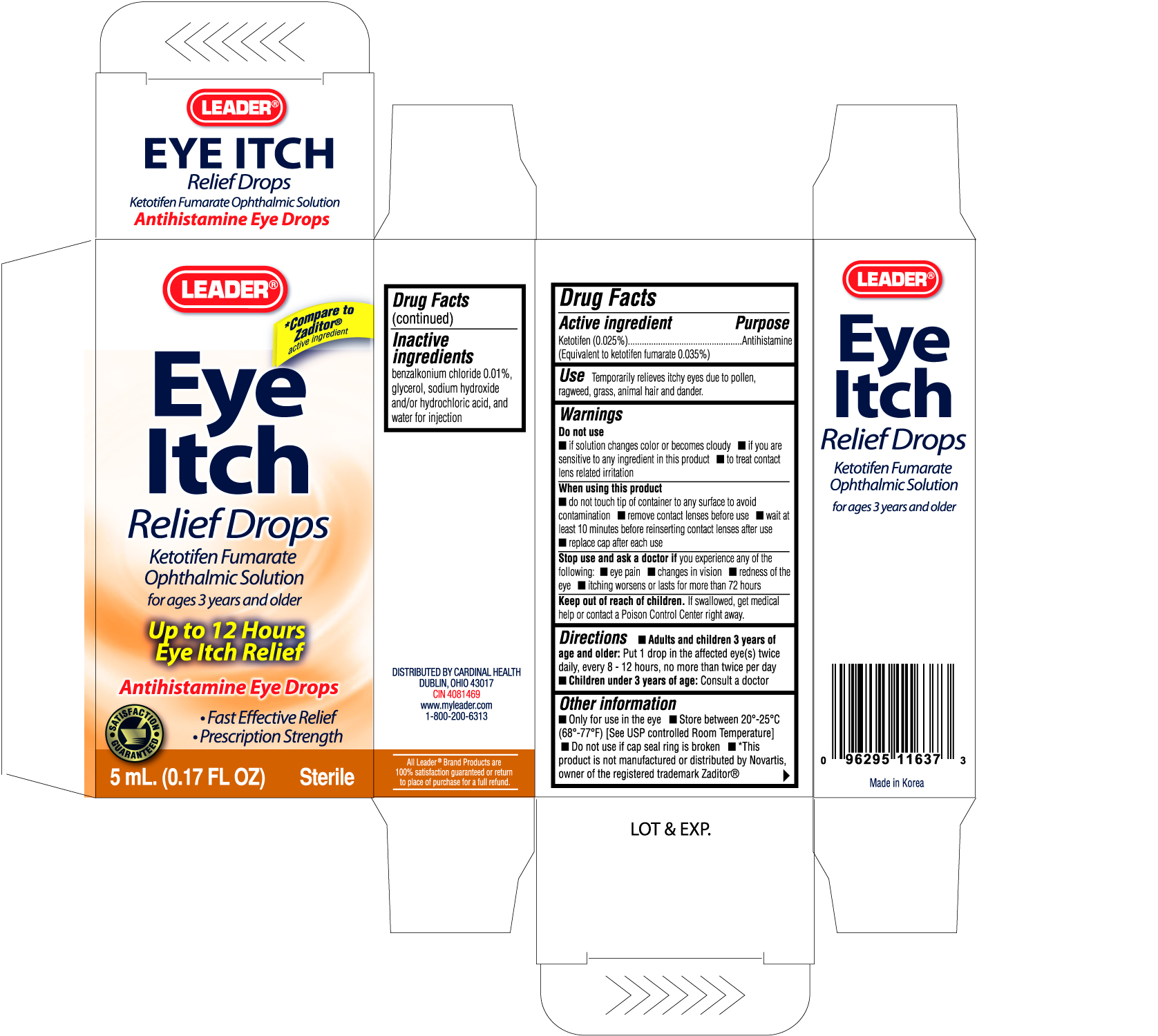 DRUG LABEL: LEADER EYE ITCH RELIEF DROPS
NDC: 11716-1163 | Form: SOLUTION/ DROPS
Manufacturer: HANLIM PHARM. CO., LTD.
Category: otc | Type: HUMAN OTC DRUG LABEL
Date: 20100421

ACTIVE INGREDIENTS: KETOTIFEN FUMARATE 0.345 mg/1 mL
INACTIVE INGREDIENTS: BENZALKONIUM CHLORIDE; GLYCERIN; SODIUM HYDROXIDE; WATER

Drug Facts

Active ingredient Purpose

Ketotifen (0.025%)..........................................Antihistamine

(Equivalent to ketotifen fumarate 0.035%)

Use

Temporarily relieves itchy eyes due to pollen, ragweed, grass, animal hair and dander.

Warnings

Do not use

- if solution changes color or becomes cloudy
- if you are sensitive to any ingredient in this product
- to treat contact lens related irritation

When using this product

- do not touch tip of container to any surface to avoid contamination
- remove contact lenses before use
- wait at least 10 minutes before reinserting contact lenses after use
- replace cap after each use

Stop use and ask a doctor if you experience any of the following:

- eye pain
- changes in vision
- redness of the eye
- itching worsens or lasts for more than 72 hours

Keep out of reach of children. If swallowed, get medical help or contact a Poison Control Center right away.

Directions

- Adults and children 3 years of age and older: Put 1 drop in the affected eye(s) twice daily, every 8-12 hours, no more than twice per day
- Children under 3 years of age: Consult a doctor

Other information

- Only for use in the eye
- Store between 20o-25oC (68o to 77oF) (See USP controlled Room Temperature)
- Do not use if cap seal ring is broken

Inactive ingredients

benzalkonium chloride 0.01%, glycerol, sodium hydroxide and/or hydrochloric acid, and water for injection

PACKAGE LABEL

Enter section text here